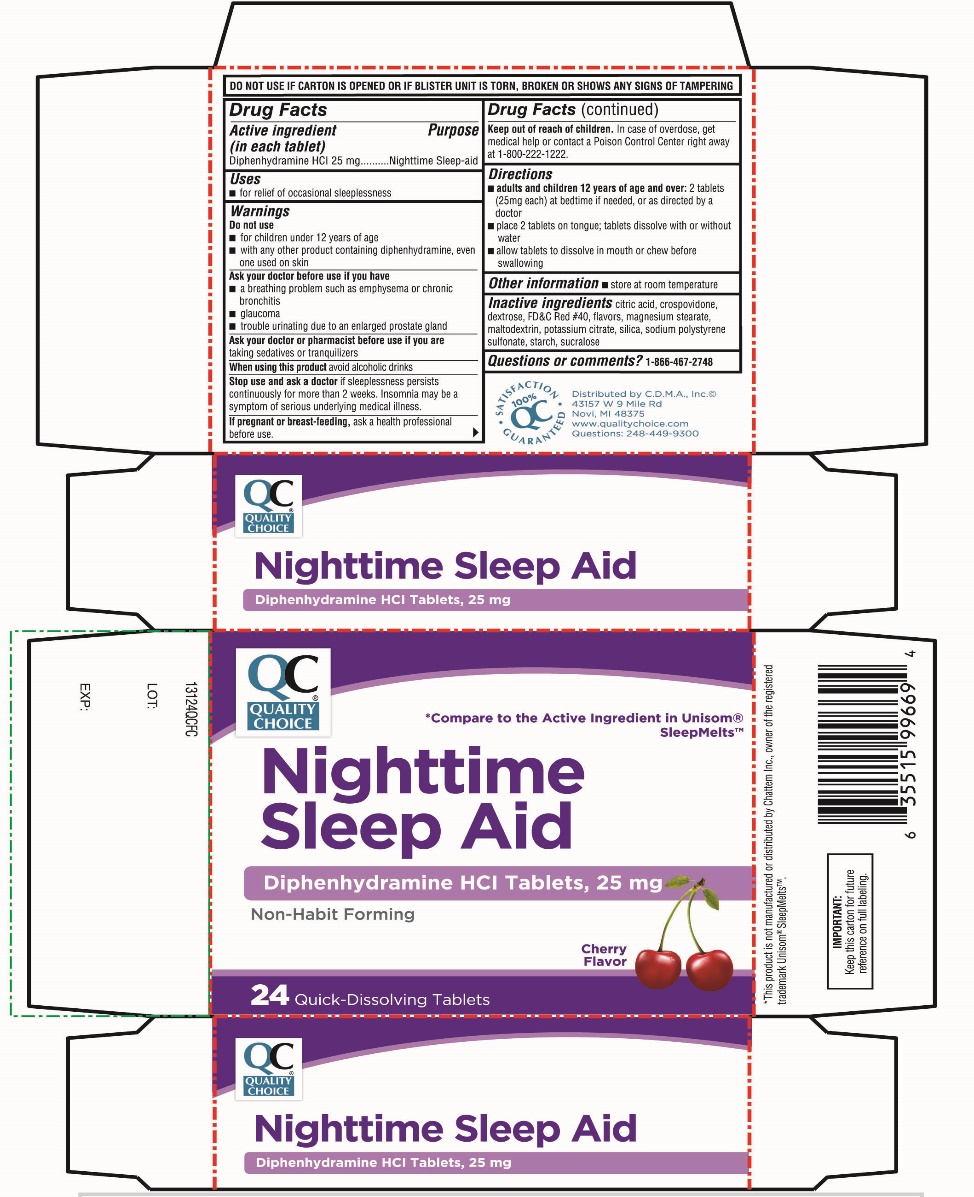 DRUG LABEL: Unisom SleepMelts Nighttime Sleep-Aid
NDC: 63868-393 | Form: TABLET, CHEWABLE
Manufacturer: QUALITY CHOICE (CHAIN DRUG MARKETING ASSOCIATION)
Category: otc | Type: HUMAN OTC DRUG LABEL
Date: 20251204

ACTIVE INGREDIENTS: DIPHENHYDRAMINE HYDROCHLORIDE 25 mg/1 1
INACTIVE INGREDIENTS: CITRIC ACID MONOHYDRATE; CROSPOVIDONE (120 .MU.M); DEXTROSE, UNSPECIFIED FORM; FD&C RED NO. 40; MAGNESIUM STEARATE; MALTODEXTRIN; POTASSIUM CITRATE; SILICON DIOXIDE; SODIUM POLYSTYRENE SULFONATE; STARCH, CORN; SUCRALOSE

Unisom Sleep Melts Nighttime Sleep-Aid

Drug Facts

Active ingredient

(in each caplet)

Diphenhydramine HCI 25 mg

Purpose

Nighttime sleep-aid

Uses

- for relief of occasional sleeplessness

Warnings

Do not use

- for children under 12 years of age
- with any other product containing diphenhydramine, even one used on skin

Ask a doctor before use if you have

- a breathing problem such as emphysema or chronic bronchitis
- glaucoma
- trouble urinating due to an enlarged prostate gland

Ask a doctor or pharmacist before use if you are

taking sedatives or tranquilizers

When using this product

avoid alcoholic drinks

Stop use and ask a doctor if

sleeplessness persists continuously for more than 2 weeks. Insomnia may be a symptom of serious underlying medical illness.

If pregnant or breast-feeding,

ask a health professional before use.

Keep out of reach of children.

In case of overdose, get medical help or contact a Poison Control Center right away at 1-800-222-1222.

Directions

- adults and children 12 years of age and over:2 tablets (25 mg each) at bedtime if needed, or as directed by a doctor
- place 2 tablets on tongue; tablets dissolve with or without water
- allow tablets to dissolve in mouth or chew before swallowing

Other Information

- store at room temperature

Inactive ingredients

citric acid, crospovidone, dextrose. FD&C RED # 40, flavor, magnesium stearate, maltodextrin, potassium citrate, silica, sodium polystyrene sulfonate, starch, sucralose.

Questions or comments?

1-866-467-2748

PRINCIPAL DISPLAY PANEL

* Compare to the Active Ingredient in Unisom® SleepMelts™

Nighttime Sleep Aid
Diphenhydramine HCI Tablets, 25 mg
24 Quick-Dissolving Tablets

Non-Habit Forming

Cherry Flavor

100% SATISFACTION GUARANTEED

Distributed By C.D.M.A., Inc.©

43157 W 9 Mile Rd

Novi, MI 48375

www.qualitychoice.com

Questions: 248-449-9300

DO NOT USE IF CARTON IS OPENED OR IF BLISTER UNIT IS TORN, BROKEN OR SHOWS ANY SIGNS OF TEMPERING.

*This product is not manufactured or distributed by Chattern Inc., owner of the registered trademark Unisom® SleepMelts™